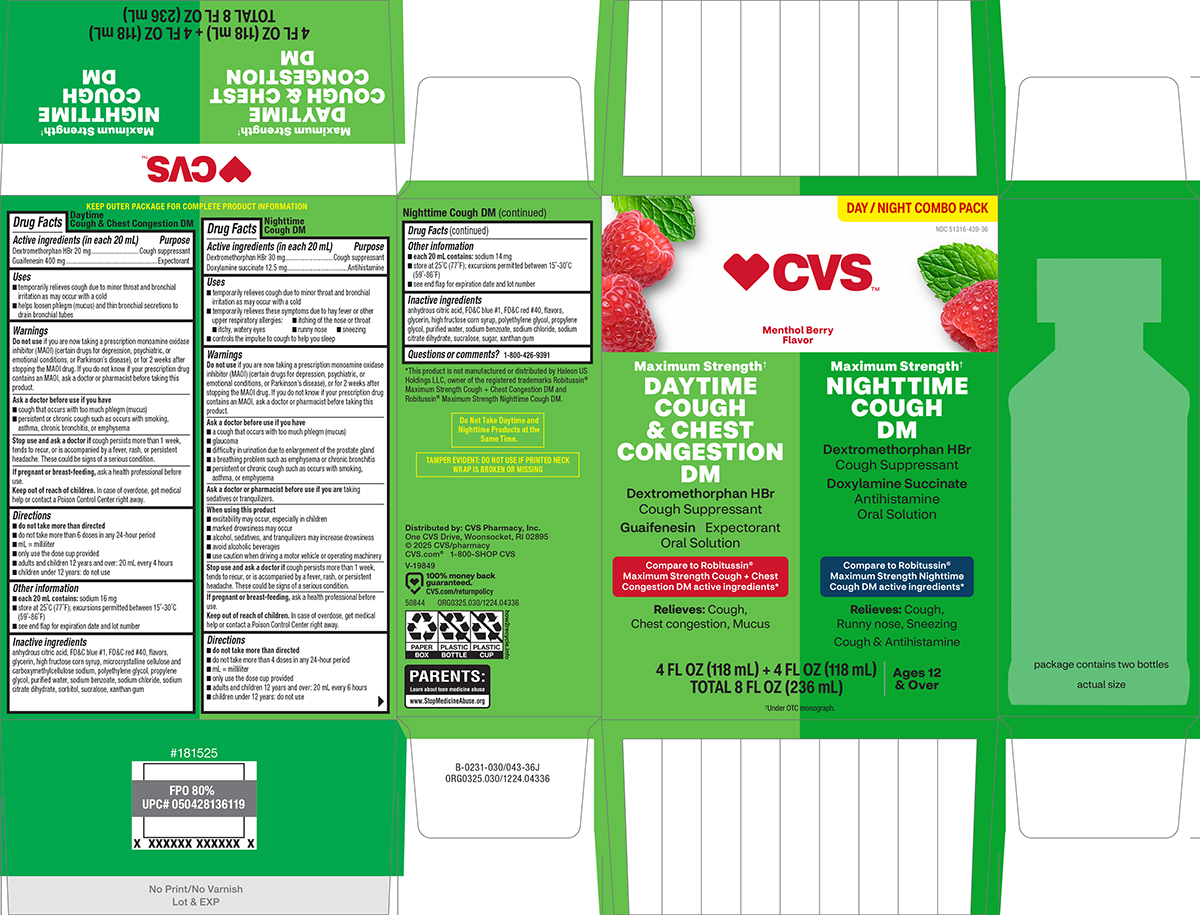 DRUG LABEL: Cough and Chest Congestion DN, Cough DM
NDC: 51316-439 | Form: KIT | Route: ORAL
Manufacturer: CVS WOONSOCKET PRESCRIPTION CENTER, INCORPORATED
Category: otc | Type: HUMAN OTC DRUG LABEL
Date: 20260225

ACTIVE INGREDIENTS: DEXTROMETHORPHAN HYDROBROMIDE 20 mg/20 mL; GUAIFENESIN 400 mg/20 mL; DEXTROMETHORPHAN HYDROBROMIDE 30 mg/20 mL; DOXYLAMINE SUCCINATE 12.5 mg/20 mL
INACTIVE INGREDIENTS: ANHYDROUS CITRIC ACID; FD&C BLUE NO. 1; FD&C RED NO. 40; GLYCERIN; HIGH FRUCTOSE CORN SYRUP; MICROCRYSTALLINE CELLULOSE; CARBOXYMETHYLCELLULOSE SODIUM, UNSPECIFIED; POLYETHYLENE GLYCOL, UNSPECIFIED; PROPYLENE GLYCOL; WATER; SODIUM BENZOATE; SODIUM CHLORIDE; TRISODIUM CITRATE DIHYDRATE; SORBITOL; SUCRALOSE; XANTHAN GUM; ANHYDROUS CITRIC ACID; FD&C BLUE NO. 1; FD&C RED NO. 40; GLYCERIN; HIGH FRUCTOSE CORN SYRUP; POLYETHYLENE GLYCOL, UNSPECIFIED; PROPYLENE GLYCOL; WATER; SODIUM BENZOATE; SODIUM CHLORIDE; TRISODIUM CITRATE DIHYDRATE; SUCRALOSE; SUCROSE; XANTHAN GUM

CVS 44-030043

Day

Active ingredients (in each 20 mL)

Dextromethorphan HBr 20 mg
Guaifenesin 400 mg

Purpose

Cough suppressant
Expectorant

Uses

- temporarily relieves cough due to minor throat and bronchial irritation as may occur with a cold
- helps loosen phlegm (mucus) and thin bronchial secretions to drain bronchial tubes

Warnings

Do not use

if you are now taking a prescription monoamine oxidase inhibitor (MAOI) (certain drugs for depression, psychiatric, or emotional conditions, or Parkinson’s disease), or for 2 weeks after stopping the MAOI drug. If you do not know if your prescription drug contains an MAOI, ask a doctor or pharmacist before taking this product.

Ask a doctor before use if you have

- cough that occurs with too much phlegm (mucus)
- persistent or chronic cough such as occurs with smoking, asthma, chronic bronchitis, or emphysema

Stop use and ask a doctor if

cough persists more than 1 week, tends to recur, or is accompanied by a fever, rash, or persistent headache. These could be signs of a serious condition.

If pregnant or breast-feeding

ask a health professional before use.

Keep out of reach of children.

In case of overdose, get medical help or contact a Poison Control Center right away.

Directions

- do not take more than directed
- do not take more than 6 doses in any 24-hour period
- mL = milliliter
- only use the dose cup provided
- adults and children 12 years and over: 20 mL every 4 hours
- children under 12 years: do not use

Other information

- each 20 mL contains: sodium 16 mg
- store at 25°C (77°F); excursions permitted between 15°-30°C (59°-86°F)
- see end flap for expiration date and lot number

Inactive ingredients

anhydrous citric acid, FD&C blue #1, FD&C red #40, flavors, glycerin, high fructose corn syrup, microcrystalline cellulose and carboxymethylcellulose sodium, polyethylene glycol, propylene glycol, purified water, sodium benzoate, sodium chloride, sodium citrate dihydrate, sorbitol, sucralose, xanthan gum

Night

Active ingredients (in each 20 mL)

Dextromethorphan HBr 30 mg
Doxylamine succinate 12.5 mg

Purpose

Cough suppressant
Antihistamine

Uses

- temporarily relieves cough due to minor throat and bronchial irritation as may occur with a cold
- temporarily relieves these symptoms due to hay fever or other upper respiratory allergies:
  - itching of the nose or throat
  - itchy, watery eyes
  - runny nose
  - sneezing
- controls the impulse to cough to help you sleep

Warnings

Do not use

if you are now taking a prescription monoamine oxidase inhibitor (MAOI) (certain drugs for depression, psychiatric, or emotional conditions, or Parkinson’s disease), or for 2 weeks after stopping the MAOI drug. If you do not know if your prescription drug contains an MAOI, ask a doctor or pharmacist before taking this product.

Ask a doctor before use if you have

- a cough that occurs with too much phlegm (mucus)
- glaucoma
- difficulty in urination due to enlargement of the prostate gland
- a breathing problem such as emphysema or chronic bronchitis
- persistent or chronic cough such as occurs with smoking, asthma, or emphysema

Ask a doctor or pharmacist before use if you are

taking sedatives or tranquilizers.

When using this product

- marked drowsiness may occur
- avoid alcoholic beverages
- alcohol, sedatives, and tranquilizers may increase drowsiness
- use caution when driving a motor vehicle or operating machinery
- excitability may occur, especially in children

Stop use and ask a doctor if

cough persists more than 1 week, tends to recur, or is accompanied by a fever, rash, or persistent headache. These could be signs of a serious condition.

If pregnant or breast-feeding,

ask a health professional before use.

Keep out of reach of children.

In case of overdose, get medical help or contact a Poison Control Center right away.

Directions

- do not take more than directed
- do not take more than 4 doses in any 24-hour period
- mL = milliliter
- only use the dose cup provided
- adults and children 12 years and over: 20 mL every 6 hours
- children under 12 years: do not use

Other information

- each 20 mL contains: sodium 14 mg
- store at 25ºC (77ºF); excursions permitted between 15º-30ºC (59º-86ºF)
- see end flap for expiration date and lot number

Inactive ingredients

anhydrous citric acid, FD&C blue #1, FD&C red #40, flavors, glycerin, high fructose corn syrup, polyethylene glycol, propylene glycol, purified water, sodium benzoate, sodium chloride, sodium citrate dihydrate, sucralose, sugar, xanthan gum

Questions or comments?

1-800-426-9391

Principal Display Panel

♥CVS™

DAY / NIGHT COMBO PACK

NDC 51316-439-36

Menthol Berry
Flavor

Maximum Strength†

DAYTIME
COUGH
& CHEST
CONGESTION
DM

Dextromethorphan HBr
Cough Suppressant
Guaifenesin | Expectorant
Oral Solution

Compare to Robitussin®
Maximum Strength Cough + Chest
Congestion DM active ingredients*

Relieves: Cough,
Chest congestion, Mucus

Maximum Strength†

NIGHTTIME
COUGH
DM

Dextromethorphan HBr
Cough Suppressant
Doxylamine Succinate
Antihistamine
Oral Solution

Compare to Robitussin®
Maximum Strength Nighttime
Cough DM active ingredients*

Relieves: Cough,
Runny nose, Sneezing
Cough & Antihistamine

4 FL OZ (118 mL) + 4 FL OZ (118 mL)
TOTAL 8 FL OZ (236 mL)

Ages 12
& Over

†Under OTC monograph.

Do Not Take Daytime and
Nighttime Products at the
Same Time.

TAMPER EVIDENT: DO NOT USE IF PRINTED NECK
WRAP IS BROKEN OR MISSING

*This product is not manufactured or distributed by Haleon US
Holdings LLC, owner of the registered trademarks Robitussin®
Maximum Strength Cough + Chest Congestion DM and
Robitussin® Maximum Strength Nighttime Cough DM.

Distributed by: CVS Pharmacy, Inc.
One CVS Drive, Woonsocket, RI 02895
© 2025 CVS/pharmacy
CVS.com® 1-800-SHOP CVS
V-19849

50844 ORG0325.030/1224.04336

PARENTS:
Learn about teen medicine abuse
www.StopMedicineAbuse.org

100% money back
guaranteed.
CVS.com/returnpolicy

CVS 44-030043